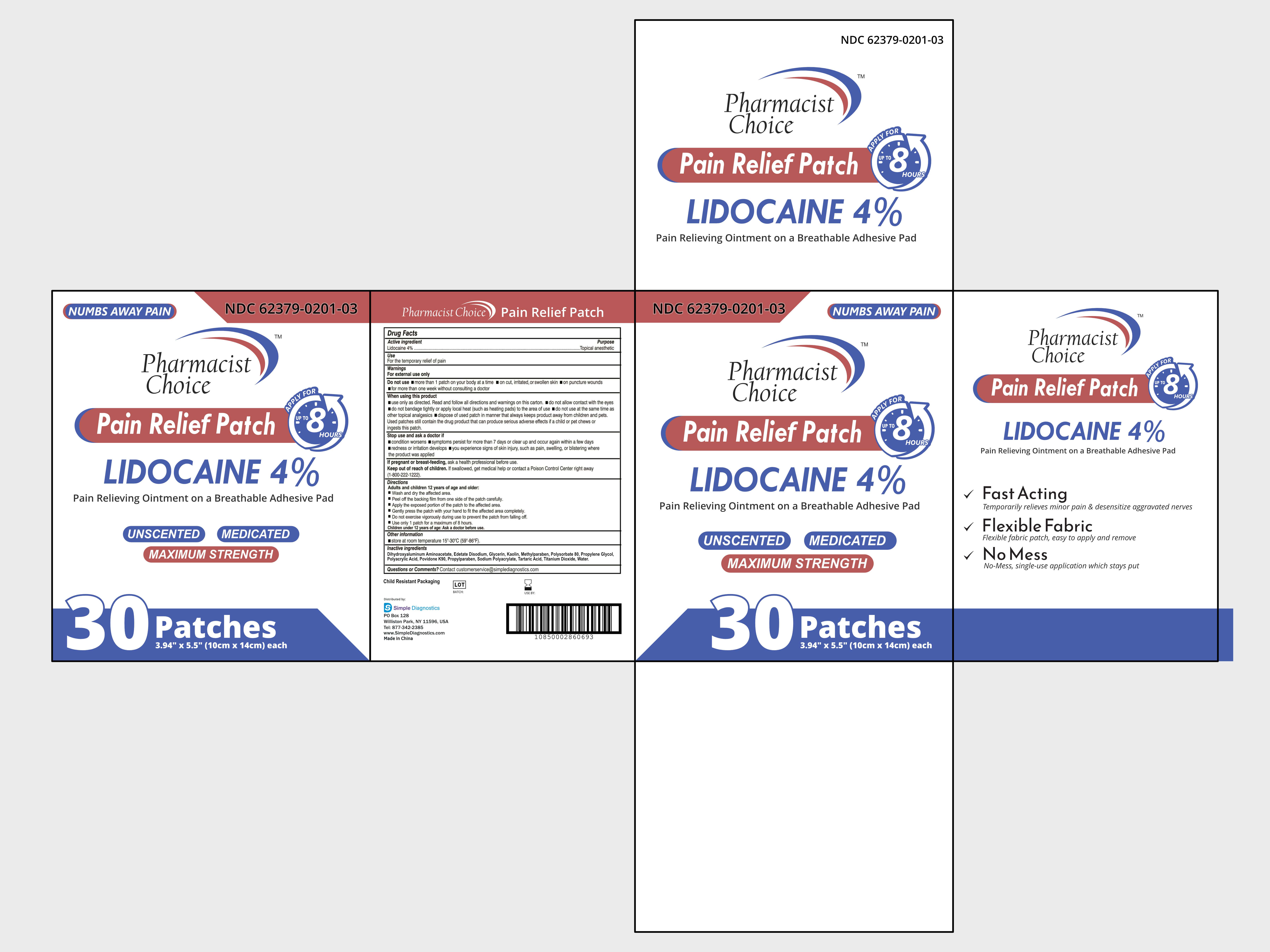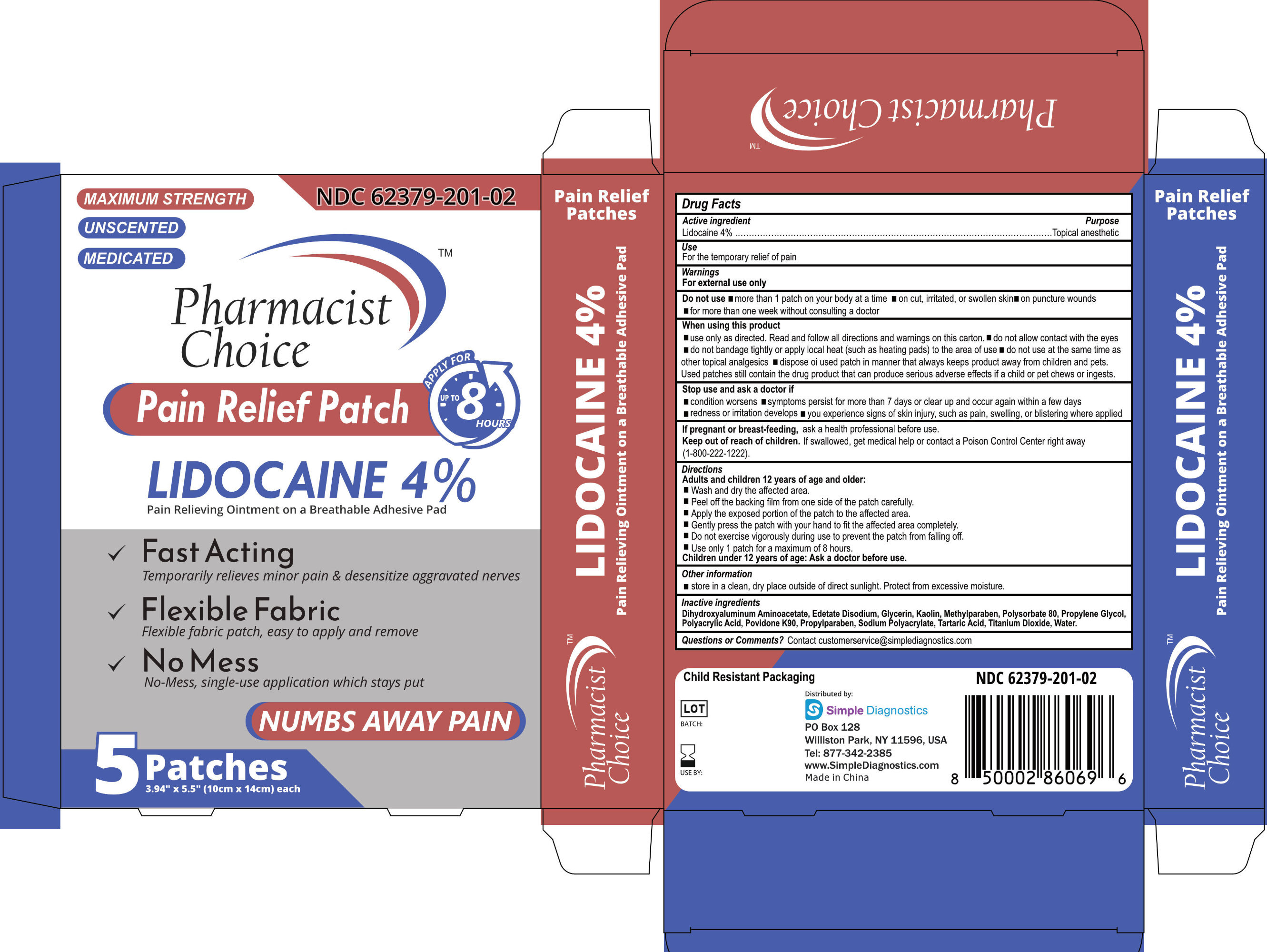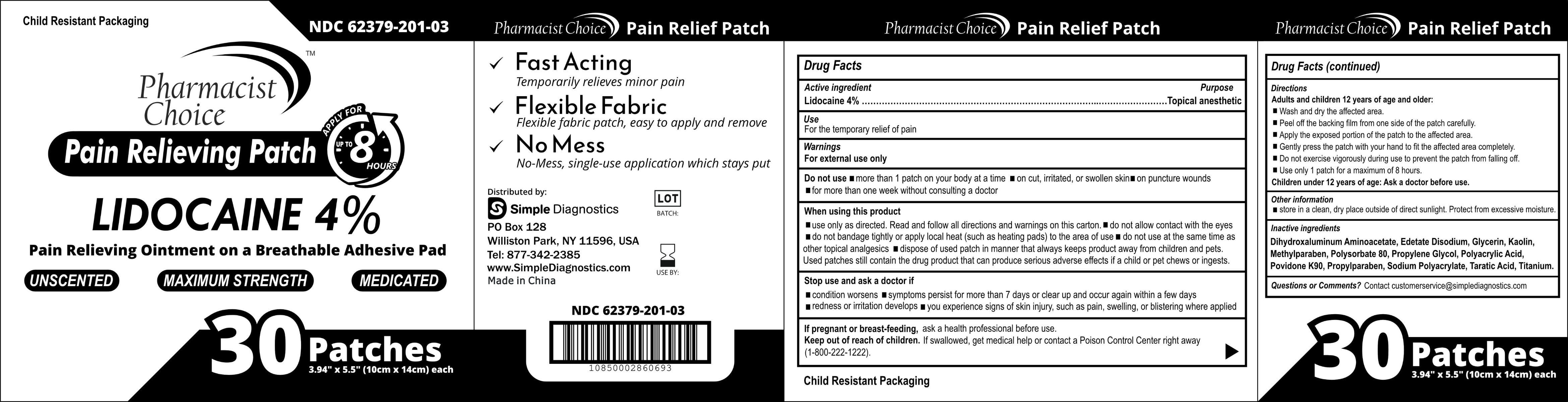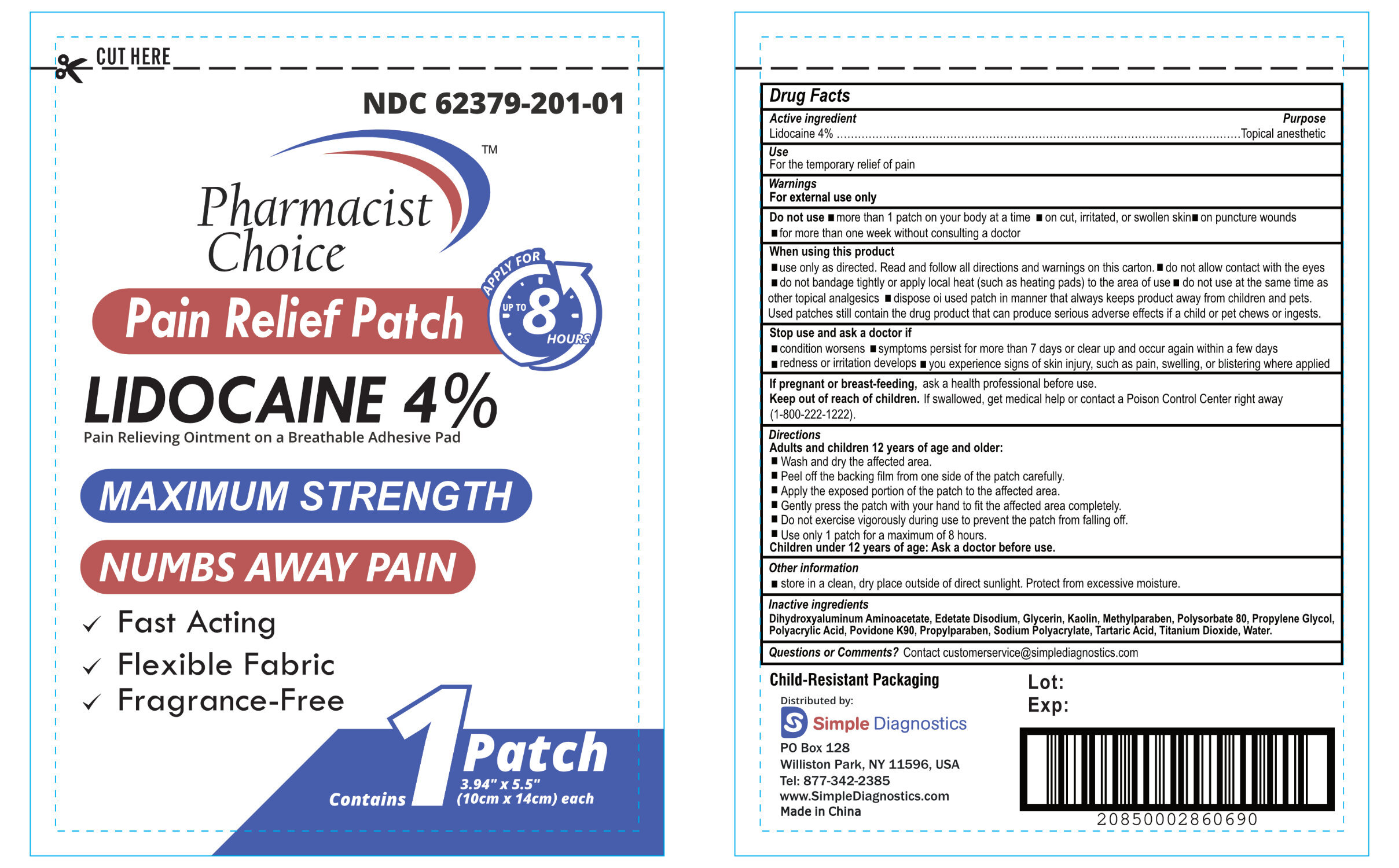 DRUG LABEL: Pain Reliveing Patch
NDC: 62379-201 | Form: PATCH
Manufacturer: simple diagnostics
Category: otc | Type: HUMAN OTC DRUG LABEL
Date: 20250207

ACTIVE INGREDIENTS: LIDOCAINE 0.4 g/1 1
INACTIVE INGREDIENTS: KAOLIN; PROPYLPARABEN; SODIUM POLYACRYLATE (2500000 MW); POVIDONE K90; EDETATE DISODIUM; METHYLPARABEN; TITANIUM DIOXIDE; DIHYDROXYALUMINUM AMINOACETATE ANHYDROUS; PROPYLENE GLYCOL; POLYACRYLIC ACID (250000 MW); TARTARIC ACID; WATER; GLYCERIN; POLYSORBATE 80

Pain Relieving Patch

Drug Facts

LIDOCAINE PATCH 4%

Active Ingredient

Lidocaine 4%

Purpose

Topical anesthetic

USE

For the temporary relief of pain

Warnings

For external use only

Do not use more than 1 patch on vour bodv at a time on cut, irritated.or swolen skin on puncture wounds
for more than one week without consulting a doctor

When using this product

Use only as directed. Read and follow all directions and warnings on this carton. do not allow contact with the eyes
do not bandage tightly or apply local heat (such as heating pads) to the area of use do not use at the same time as other topical analcesics
dispose of used patch in manner that always keeps product away from children and pets. Used patches still contain the drug product that can produce serious adverse effects if a child or pet chews or ingests this patch.

DO NOT USE:

- More than 1 patch at a time
- On wounds or damaged skin
- For more than one week without consulting a doctor
- If you are allergic to any ingredients of this product

STOP USE AND ASK A DOCTOR IF:

- Localized skin reactions occur, such as rash, itching, redness, irritation, pain, swelling and blistering
- Condition worsen
- Symptoms persist for more than 7 days
- Symptoms clear up and occur again within a few days

IF PREGNANT OR BREAST-FEEDING:

Ask a health professional before use

Keep out of reach of children

If swallowed, get medical help or contact a Poison Control Center right away(1-800-222-1222).

Directions

Adults and children 12 years of age and older:
Wash and dry the affected area.
Peel off the backing film from one side of the patch carefully
Apply the exposed portion of the patch to the affected area.
Gently press the patch with your hand to fit the affected area completely.
Do not exercise vigorously during use to prevent the patch from falling off.
Use only 1 patch for a maximum of 8 hours.
Children under 12 years of age: Ask a doctor before use.

QUESTIONS OR COMMENTS:

- Customerservice@simplediagnostics.com
- 877-342-2385

Other information

- Store at room temperature 15°-30°C (59°-86°F)
- Store in a cool dry place away from direct sunlight

Inactive ingredient

Dihydroxyaluminum Aminoacetate, Edetate Disodium, Glycerin, Kaolin, Methylparaben, Polysorbate 80, Propylene Glycol, Polyacrylic Acid, Povidone K90, Propylparaben, Sodium Polyacrylate, Tartaric Acid, Titanium Dioxide, Water.